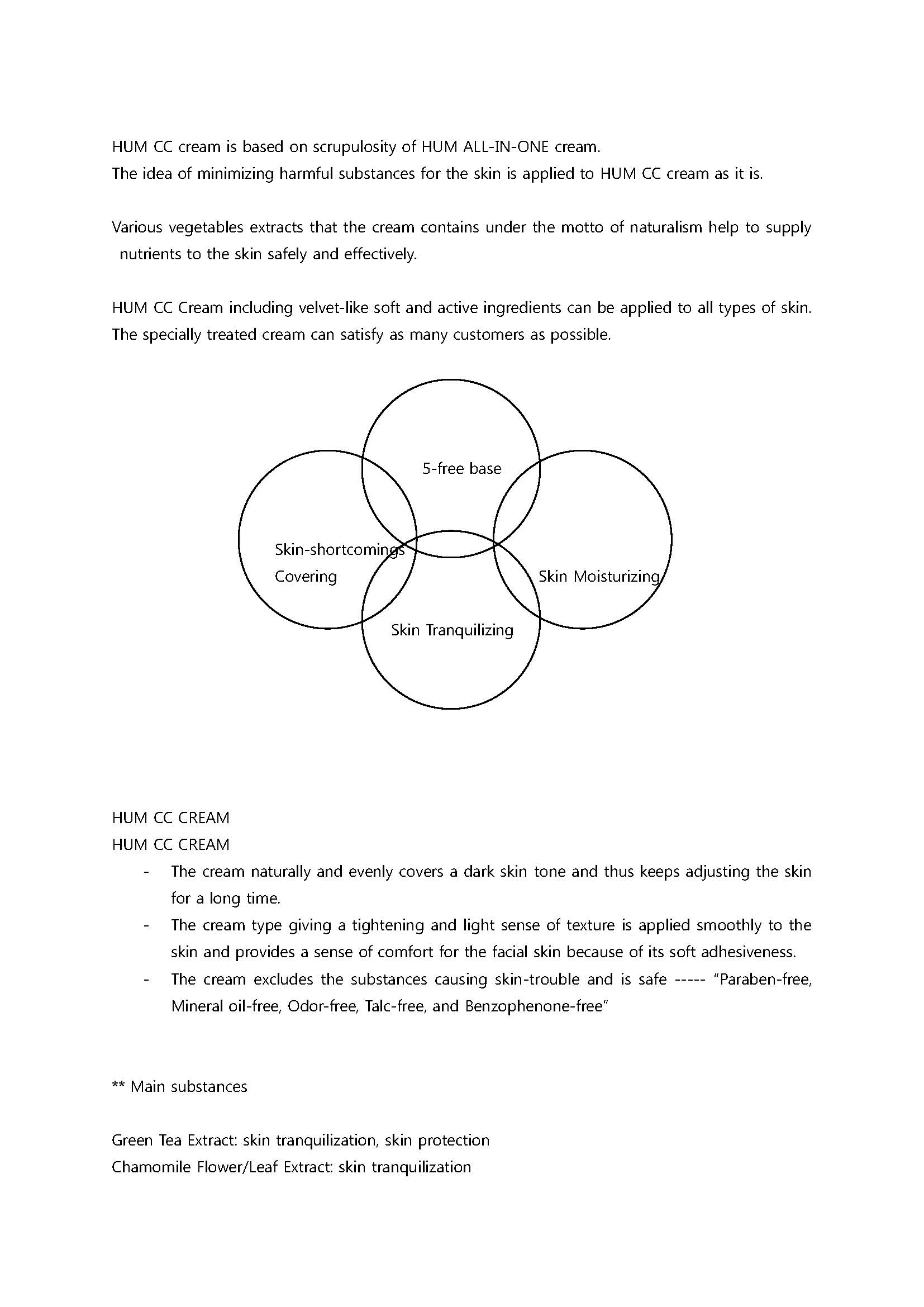 DRUG LABEL: Hum CC
NDC: 61254-3001 | Form: CREAM
Manufacturer: Happy Sonic Global Co., Ltd.
Category: otc | Type: HUMAN OTC DRUG LABEL
Date: 20140302

ACTIVE INGREDIENTS: GLYCERIN 0.1 g/100 g
INACTIVE INGREDIENTS: SORBITAN SESQUIOLEATE; CYCLOMETHICONE 5; TITANIUM DIOXIDE

Drug Facts

ACTIVE INGREDIENT

glycerin

INACTIVE INGREDIENT

Purified water, Caprlic and Capric Triglycerid, Titanium dioxide, Glycerin(e), Ethylhexyl Methoxycinnamate, Zinc oxid, Cyclopentasiloxane, CETYL PEG/PPG-10/1 Demethicone, Sorbitan Sesquioleate, Cyclohexasiloxane, Cyclomethicone, Yellow Iron Oxide, 4-Methylbenzylidene Camphor, Sodium Chloride, Red Iron Oxide, Hydroxyethylcellulose, Dimethicone/Vinyl Dimethicone Crosspolymer, Phenoxyethanol, Black Iron Oxide, Magnesium Aluminum Silicate, Triethoxycaprylylsilane, PEG/PPG-19/19 Demethicone, Adenosine, Green Tea Extract, Chamomile Flower/Leaf Extract, Scutellaria Baicalensis Georgi Extract, Reynoutria Japonica Extract, Licorice Extract, Centella Asiatica Extract, Sodium Hyaluronate, Corallina Officinalis Extract

PURPOSE

skin protectant

keep out of reach of the children

INDICATIONS AND USAGE

At the last step of basic skin-care or after HUM ALL-IN-ONE cream, softly apply as needed to the entire face along the skin texture.

WARNINGS

A. Please stop using the product in anyone of the following cases:
1) Rash, swelling, itching, irritation, and other abnormal reactions on the skin after using the product.
2) When the abnormalities above appear on the skin due to direct sunlight, etc.
B. Do NOT use on a scar, or skin affected by dermatitis, eczema, etc.
C. Notes for Storage
1) Make sure to close the lid after use.
2) Keep away from babies and children.
3) Do not store in high/low temperature or under direct sun light.
Abnormal products will be compensated for according to “Standard for Consumer Dispute Resolution” by Fair Trade Commission

DOSAGE AND ADMINISTRATION

for topical use only